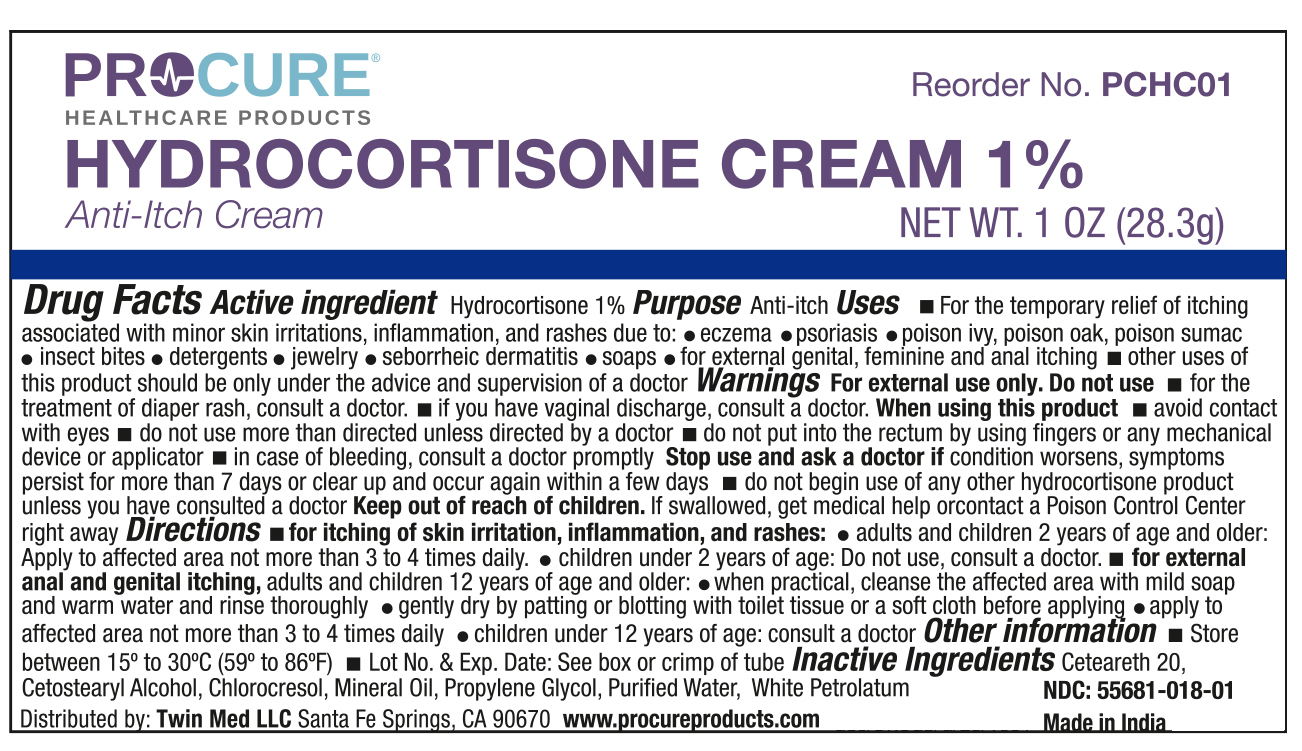 DRUG LABEL: ProCure Hydrocortisone 1%
NDC: 55681-018 | Form: CREAM
Manufacturer: Twin Med LLC
Category: otc | Type: HUMAN OTC DRUG LABEL
Date: 20250617

ACTIVE INGREDIENTS: HYDROCORTISONE 1 g/100 g
INACTIVE INGREDIENTS: WHITE PETROLATUM; PROPYLENE GLYCOL; WATER; CETEARETH-20; CETEARYL ALCOHOL; CHLOROCRESOL; MINERAL OIL

Active Ingredient

Active Ingredient: Hydrocortisone 1%

Uses

- For the temporary relief of itching associated with minor skin irritations, inflammaion, and rashes due to: eczema, psoriasis, poison ivy, poison oak, poison sumac, insect bites, detergents, jewelry, seborrheic dermatitis, soaps, and for externam genital, feminine and anal itching
- other uses of this product should be only used under the advise and supervision of a doctor

Purpose

Anti-Itch

Warnings

For external use only

Do not use

- for the treatment of diaper rash, consult a doctor
- if you have vaginal discharge, consult a doctor

When using this product

- avoid contact with eyes
- do not use more than directed unless directed by a doctor
- do not put into the rectum by using fingers or any mechanical device or applicator
- in case of bleeding, consult a doctor promptly

Stop use and ask a doctor if

- condition worsens, symptoms persist for more than 7 days or clear up and occur again within a few days
- do not begin use of any other hydrocortisone products unless you have consulted a doctor

Keep out of reach of children. If swallowed, get medical help right away or contact a Poison Control Center

Directions

For itching of skin irritation, inflammation, and rashes:

- Adults and children 2 years of age and older: apply to affected area not more than 3 to 4 times daily.
- Children under 2 years of age: do not use, consult a doctor

For external anal and genital itching:

Adults and children 12 years of age and older:

- when practical, cleanse the affected area with mild soap and warm water and rinse thoroughly
- gently dry by patting or blotting with toiet tissue or a soft cloth before apply
- apply to affected ara not more than 3 to 4 ties daily

Children under 12 years og age: consult a doctor

Inactive Ingredients

Inactive Ingredients: Ceteareth 20, Cetostearyl Alcohol, Chlorocresol, Mineral Oil, Propylene Glycol, Purified Water, White Petrolatum